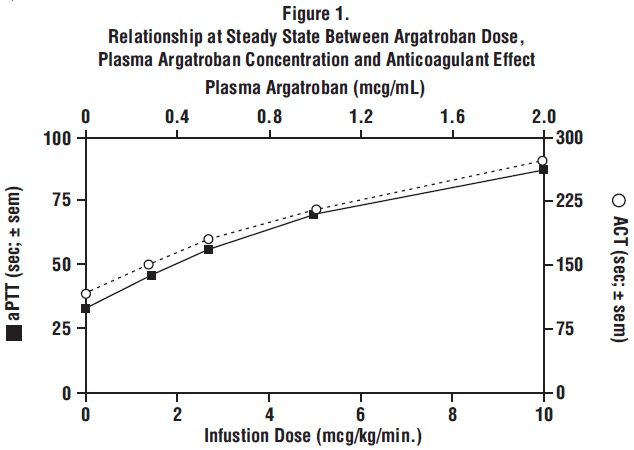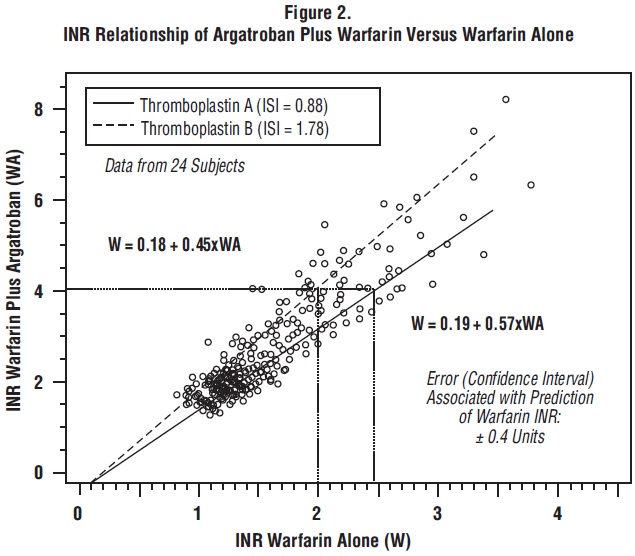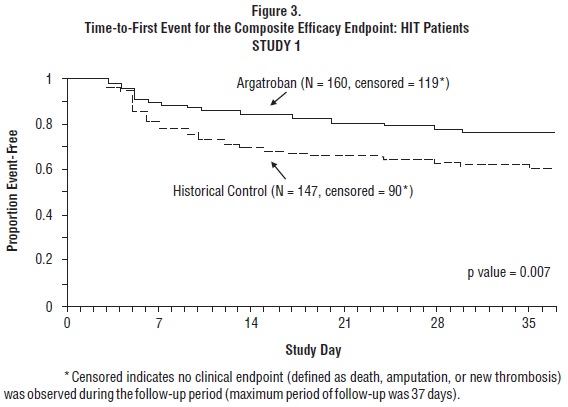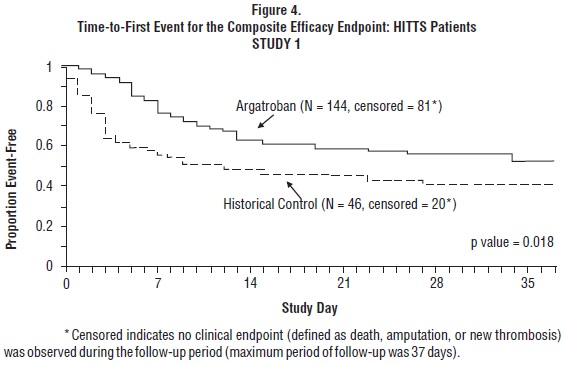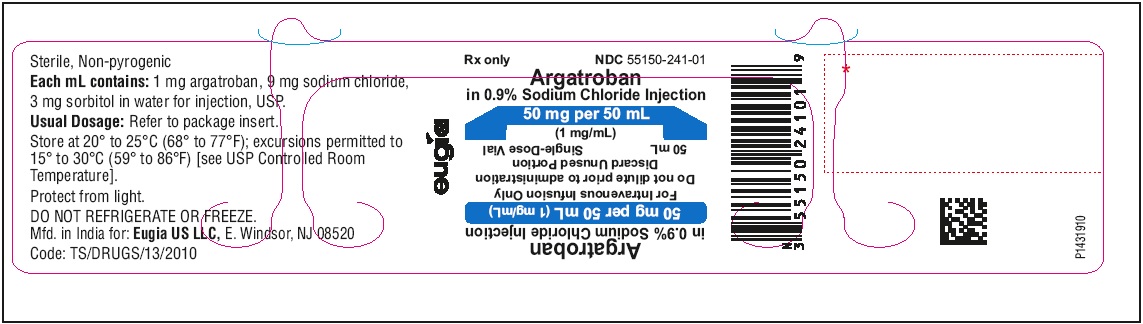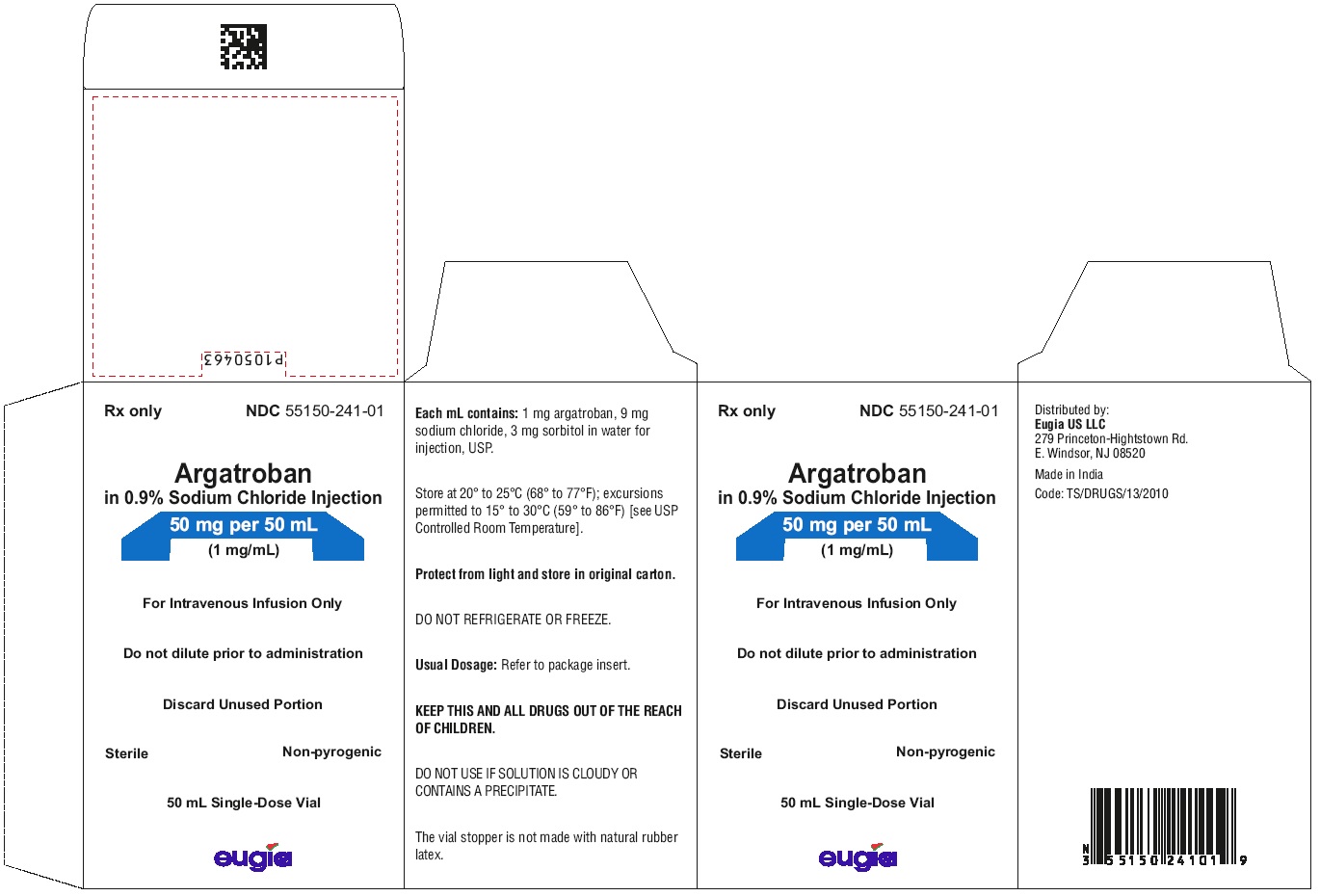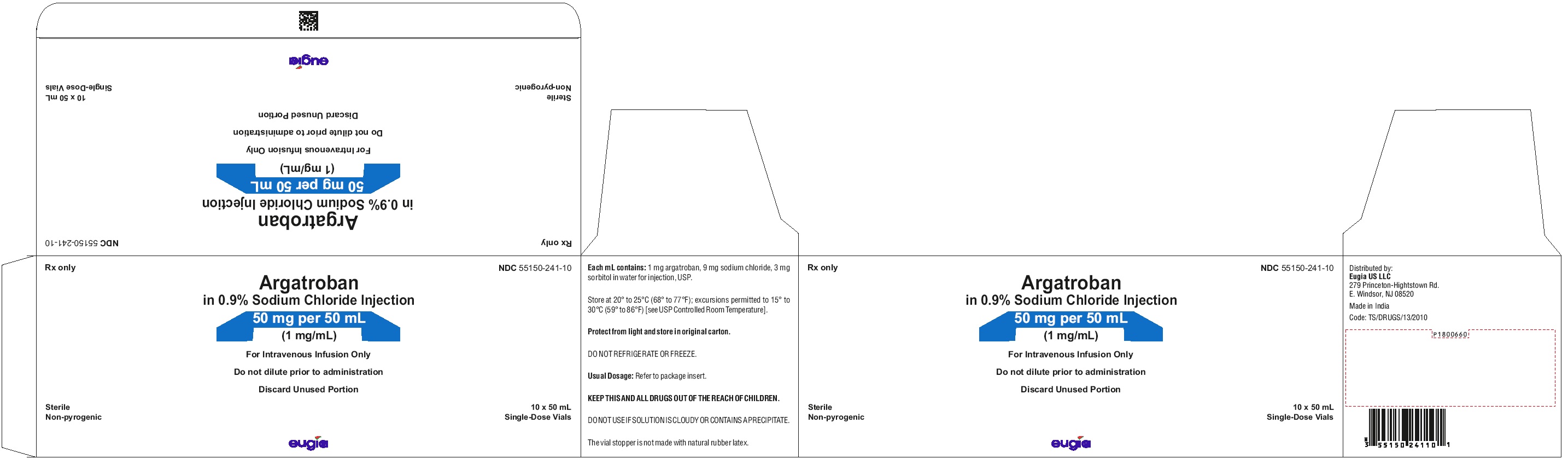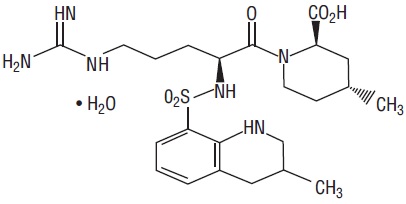 DRUG LABEL: Argatroban
NDC: 55150-241 | Form: INJECTION, SOLUTION
Manufacturer: Eugia US LLC
Category: prescription | Type: Human Prescription Drug Label
Date: 20230803

ACTIVE INGREDIENTS: ARGATROBAN 50 mg/50 mL
INACTIVE INGREDIENTS: SODIUM CHLORIDE; SORBITOL; WATER

HIGHLIGHTS OF PRESCRIBING INFORMATION

These highlights do not include all the information needed to use ARGATROBAN IN SODIUM CHLORIDE INJECTION safely and effectively. See full prescribing information for ARGATROBAN IN SODIUM CHLORIDE INJECTION.
ARGATROBAN in sodium chloride injection, for intravenous use
Initial U.S. Approval: 2000

1 INDICATIONS AND USAGE

Argatroban in sodium chloride injection is a direct thrombin inhibitor indicated:

- For prophylaxis or treatment of thrombosis in adult patients with heparin-induced thrombocytopenia (HIT) (1.1)
- As an anticoagulant in adult patients with or at risk for HIT undergoing percutaneous coronary intervention (PCI) (1.2)

2 DOSAGE AND ADMINISTRATION

- Argatroban 50 mg in 50 mL aqueous sodium chloride solution (1 mg/mL) is intended for administration to adult patients (2.1)

Heparin-Induced Thrombocytopenia (2.2)
The dose for heparin-induced thrombocytopenia without hepatic impairment is 2 mcg/kg/min administered as a continuous infusion (2.2)
Percutaneous Coronary Intervention (2.3)
The dose for patients with or at risk for heparin-induced thrombocytopenia undergoing percutaneous coronary intervention is started at 25 mcg/kg/min and a bolus of 350 mcg/kg administered via a large bore intravenous line over 3 to 5 minutes (2.3)

3 DOSAGE FORMS AND STRENGTHS

Injection: 50 mg/50 mL (1 mg/mL) clear solution in single-dose vial (3)

4 CONTRAINDICATIONS

- Major bleeding (4)
- History of hypersensitivity to this product (4)

5 WARNINGS AND PRECAUTIONS

- Risk of hemorrhage: Hemorrhage at any site can occur (unexplained fall in hematocrit of blood pressure or other unexplained symptom may indicate hemorrhage). Use with caution in patients at risk, including those receiving antiplatelet agents, thrombolytics, or other anticoagulants. (5.1)
- Use in hepatic impairment: Adjust starting dose and titrate carefully in patients with HIT who have moderate or severe hepatic impairment. Avoid use in PCI in patients with clinically significant hepatic impairment (5.2)

6 ADVERSE REACTIONS

- HIT patients: The most common (> 5%) adverse reactions were dyspnea, hypotension, fever, diarrhea, sepsis, and cardiac arrest (6.1)
- PCI patients: The most common (> 5%) adverse reactions were chest pain, hypotension, back pain, nausea, vomiting and headache (6.1)

To report SUSPECTED ADVERSE REACTIONS, contact Eugia US LLC at 1-866-850-2876 or FDA at 1-800-FDA-1088 or www.fda.gov/medwatch.

8 USE IN SPECIFIC POPULATIONS

- Lactation: Discontinue nursing or drug, taking into account the importance of the drug to the mother. (8.2)
- Pediatric Use: Safety and effectiveness have not been established (8.4)

FULL PRESCRIBING INFORMATION

1 INDICATIONS AND USAGE

1.1 Heparin-Induced Thrombocytopenia

Argatroban in sodium chloride injection is indicated for prophylaxis or treatment of thrombosis in adult patients with heparin-induced thrombocytopenia (HIT).

1.2 Percutaneous Coronary Intervention

Argatroban in sodium chloride injection is indicated as an anticoagulant in adult patients with or at risk for HIT undergoing percutaneous coronary intervention (PCI).

2 DOSAGE AND ADMINISTRATION

2.1 Preparation for Intravenous Administration

Each 50 mL glass vial contains 50 mg of argatroban (1 mg/mL); and, as supplied, is ready for intravenous infusion. Dilution is not required.
Argatroban in sodium chloride injection is a clear, colorless to pale yellow solution. Parenteral drug products should be inspected visually for particulate matter and discoloration prior to administration whenever solution and container permit.
Do not use if the solution is cloudy, contains precipitates, or if the cap/over seal is not intact.
Vial may be inverted for use with a medical infusion set.

2.2 Dosing in Patients with Heparin-Induced Thrombocytopenia

Initial Dosage:
Before administering Argatroban in sodium chloride injection, discontinue heparin therapy and obtain a baseline aPTT. The recommended initial dose of Argatroban in sodium chloride injection for adult patients without hepatic impairment is 2 mcg/kg/min, administered as a continuous infusion (see Table 1).

Table 1.
Recommended Doses and Infusion Rates for 2 mcg/kg/min Dose of Argatroban in Sodium Chloride Injection for Patients With HIT^1 and Without Hepatic Impairment (1 mg/mL Concentration)
Body Weight (kg) | Dose (mcg/min) | Infusion Rate (mL/hr)
50 | 100 | 6
60 | 120 | 7
70 | 140 | 8
80 | 160 | 10
90 | 180 | 11
100 | 200 | 12
110 | 220 | 13
120 | 240 | 14
130 | 260 | 16
140 | 280 | 17
1. with or without thrombosis

Monitoring Therapy:
For use in HIT, therapy with Argatroban in sodium chloride injection is monitored using the aPTT with a target range of 1.5 to 3 times the initial baseline value (not to exceed 100 seconds). Tests of anticoagulant effects (including the aPTT) typically attain steady-state levels within 1 to 3 hours following initiation of Argatroban in sodium chloride injection. Check the aPTT 2 hours after initiation of therapy and after any dose change to confirm that the patient has attained the desired therapeutic range.
Dosage Adjustment:
After the initiation of Argatroban in sodium chloride injection, adjust the dose (not to exceed 10 mcg/kg/min) as necessary to obtain a steady-state aPTT in the target range [see Clinical Studies (14.1)].

2.3 Dosing in Patients Undergoing Percutaneous Coronary Interventions

Initial Dosage:
Initiate an infusion of Argatroban in sodium chloride injection at 25 mcg/kg/min and administer a bolus of 350 mcg/kg via a large bore intravenous line over 3 to 5 minutes (see Table 2). Check an activated clotting time (ACT) 5 to 10 minutes after the bolus dose is completed. The PCI procedure may proceed if the ACT is greater than 300 seconds.
Dosage Adjustment:
If the ACT is less than 300 seconds, an additional intravenous bolus dose of 150 mcg/kg should be administered, the infusion dose increased to 30 mcg/kg/min, and the ACT checked 5 to 10 minutes later (see Table 2).
If the ACT is greater than 450 seconds, decrease the infusion rate to 15 mcg/kg/min, and check the ACT 5 to 10 minutes later (Table 3).
Continue titrating the dose until a therapeutic ACT (between 300 and 450 seconds) has been achieved; continue the same infusion rate for the duration of the PCI procedure.
In case of dissection, impending abrupt closure, thrombus formation during the procedure, or inability to achieve or maintain an ACT over 300 seconds, additional bolus doses of 150 mcg/kg may be administered and the infusion dose increased to 40 mcg/kg/min. Check the ACT after each additional bolus or change in the rate of infusion.

Table 2.
Recommended Starting and Maintenance Doses (Within the Target ACT Range) of Argatroban in Sodium Chloride Injection in Patients Undergoing PCI Without Hepatic Impairment
(1 mg/mL Concentration)
Body Weight (kg) | Starting Bolus Dose (350 mcg/kg) |  | Starting and Maintenance Continuous Infusion Dosing For ACT 300 to 450 seconds 25 mcg/kg/min
Body Weight (kg) | Bolus Dose (mcg) | Bolus Volume (mL) | Continuous Infusion Dose (mcg/min) | Continuous Infusion Rate (mL/hr)
50 | 17,500 | 18 | 1,250 | 75
60 | 21,000 | 21 | 1,500 | 90
70 | 24,500 | 25 | 1,750 | 105
80 | 28,000 | 28 | 2,000 | 120
90 | 31,500 | 32 | 2,250 | 135
100 | 35,000 | 35 | 2,500 | 150
110 | 38,500 | 39 | 2,750 | 165
120 | 42,000 | 42 | 3,000 | 180
130 | 45,500 | 46 | 3,250 | 195
140 | 49,000 | 49 | 3,500 | 210
NOTE: 1 mg = 1,000 mcg; 1 kg = 2.2 lbs

Table 3.
Recommended Dose Adjustments of Argatroban in Sodium Chloride Injection for Patients Outside of ACT Target Range Undergoing PCI Without Hepatic Impairment (1 mg/mL Concentration)
Body Weight (kg) | If ACT Less than 300 seconds Dosage Adjustment^1 30 mcg/kg/min |  |  |  | If ACT Greater than 450 seconds Dosage Adjustment^2 15 mcg/kg/min
Body Weight (kg) | Additional Bolus Dose (mcg) | Bolus Volume (mL) | Continuous Infusion Dose (mcg/min) | Continuous Infusion Rate (mL/hr) | Continuous Infusion Dose (mcg/min) | Continuous Infusion Rate (mL/hr)
50 | 7,500 | 8 | 1,500 | 90 | 750 | 45
60 | 9,000 | 9 | 1,800 | 108 | 900 | 54
70 | 10,500 | 11 | 2,100 | 126 | 1,050 | 63
80 | 12,000 | 12 | 2,400 | 144 | 1,200 | 72
90 | 13,500 | 14 | 2,700 | 162 | 1,350 | 81
100 | 15,000 | 15 | 3,000 | 180 | 1,500 | 90
110 | 16,500 | 17 | 3,300 | 198 | 1,650 | 99
120 | 18,000 | 18 | 3,600 | 216 | 1,800 | 108
130 | 19,500 | 20 | 3,900 | 234 | 1,950 | 117
140 | 21,000 | 21 | 4,200 | 252 | 2,100 | 126
NOTE: 1 mg = 1,000 mcg; 1 kg = 2.2 lbs
1. Additional intravenous bolus dose of 150 mcg/kg should be administered if ACT less than 300 seconds.
2. No bolus dose is given if ACT greater than 450 seconds

Monitoring Therapy:
For use in PCI, therapy with Argatroban in sodium chloride injection is monitored using ACT. Obtain ACTs before dosing, 5 to 10 minutes after bolus dosing, following adjustments in the infusion rate, and at the end of the PCI procedure. Obtain additional ACTs every 20 to 30 minutes during a prolonged procedure.
Continued Anticoagulation after PCI:
If a patient requires anticoagulation after the procedure, Argatroban in sodium chloride injection may be continued, but at a rate of 2 mcg/kg/min and adjusted as needed to maintain the aPTT in the desired range [see Dosage and Administration (2.2)].

2.4 Dosing in Patients with Hepatic Impairment

For adult patients with HIT and moderate or severe hepatic impairment (based on Child-Pugh classification), an initial dose of 0.5 mcg/kg/min is recommended, based on the approximately 4-fold decrease in argatroban clearance relative to those with normal hepatic function. Monitor the aPTT closely, and adjust the dosage as clinically indicated.
Monitoring Therapy:
Achievement of steady state aPTT levels may take longer and require more dose adjustments in patients with hepatic impairment compared to patients with normal hepatic function.
For patients with hepatic impairment undergoing PCI and who have HIT or are at risk for HIT, carefully titrate Argatroban in sodium chloride injection until the desired level of anticoagulation is achieved. Use of Argatroban in sodium chloride injection in PCI patients with clinically significant hepatic disease or AST/ALT levels ≥3 times the upper limit of normal should be avoided [see Warnings and Precautions (5.2)].

2.5 Conversion to Oral Anticoagulant Therapy

Initiating Oral Anticoagulant Therapy:
When converting patients from Argatroban in sodium chloride injection to oral anticoagulant therapy, consider the potential for combined effects on International Normalized Ratio (INR). To avoid prothrombotic effects and to ensure continuous anticoagulation when initiating warfarin, overlap Argatroban in sodium chloride injection and warfarin therapy. There are insufficient data available to recommend the duration of the overlap. Initiate therapy using the expected daily dose of warfarin. A loading dose of warfarin should not be used.
The relationship between INR and bleeding risk is altered when Argatroban in sodium chloride injection and warfarin are co-administered. The combination of Argatroban in sodium chloride injection and warfarin does not cause further reduction in the vitamin K–dependent factor Xa activity than that which is seen with warfarin alone. The relationship between INR obtained on combined therapy and INR obtained on warfarin alone is dependent on both the dose of Argatroban in sodium chloride injection and the thromboplastin reagent used. The INR value on warfarin alone (INRW) can be calculated from the INR value on combination Argatroban in sodium chloride injection and warfarin therapy [see Drug Interactions (7.2) and Clinical Pharmacology (12.2)].
Co-Administration of Warfarin and Argatroban in Sodium Chloride Injection at Doses Up to 2 mcg/kg/min:
Measure INR daily while Argatroban in sodium chloride injection and warfarin are co-administered. In general, with doses of Argatroban in sodium chloride injection up to 2 mcg/kg/min, Argatroban in sodium chloride injection can be discontinued when the INR is >4 on combined therapy. After Argatroban in sodium chloride injection is discontinued, repeat the INR measurement in 4 to 6 hours. If the repeat INR is below the desired therapeutic range, resume the infusion of Argatroban in sodium chloride injection and repeat the procedure daily until the desired therapeutic range on warfarin alone is reached.
Co-Administration of Warfarin and Argatroban in Sodium Chloride Injection at Doses Greater than 2 mcg/kg/min:
For doses greater than 2 mcg/kg/min, the relationship of INR between warfarin alone to the INR on warfarin plus Argatroban in sodium chloride injection is less predictable. In this case, in order to predict the INR on warfarin alone, temporarily reduce the dose of Argatroban in sodium chloride injection to a dose of 2 mcg/kg/min. Repeat the INR on Argatroban in sodium chloride injection and warfarin 4 to 6 hours after reduction of the Argatroban in sodium chloride injection dose and follow the process outlined above for administering Argatroban in sodium chloride injection at doses up to 2 mcg/kg/min.

3 DOSAGE FORMS AND STRENGTHS

Injection: 50 mg/50 mL (1 mg/mL) clear solution in a single-dose vial. The solution is ready for intravenous infusion.

4 CONTRAINDICATIONS

Argatroban in sodium chloride injection is contraindicated in:

- Patients with major bleeding, [see Warnings and Precautions (5.1)]
- Patients with a history of hypersensitivity to argatroban products. Airway, skin, and generalized hypersensitivity reactions have been reported [see Adverse Reactions (6.1)].

5 WARNINGS AND PRECAUTIONS

5.1 Risk of Hemorrhage

Hemorrhage can occur at any site in the body in patients receiving Argatroban in sodium chloride injection. An unexplained fall in hematocrit or hemoglobin or a fall in blood pressure may indicate hemorrhage. Intracranial and retroperitoneal hemorrhage [see Adverse Reactions (6.1)] have been reported. The risk of hemorrhage with Argatroban in sodium chloride injection may be increased in severe hypertension; immediately following lumbar puncture; spinal anesthesia; major surgery (especially involving the brain, spinal cord, or eye); hematologic conditions associated with increased bleeding tendencies such as congenital or acquired bleeding disorders and gastrointestinal lesions such as ulcerations.
Concomitant use of Argatroban in sodium chloride injection with antiplatelet agents, thrombolytics, and other anticoagulants may increase the risk of bleeding.

5.2 Use in Hepatic Impairment

When administering Argatroban in sodium chloride injection to patients with hepatic impairment, start with a lower dose and carefully titrate until the desired level of anticoagulation is achieved. Achievement of steady state aPTT levels may take longer and require more Argatroban in sodium chloride injection dose adjustments in patients with hepatic impairment compared to patients with normal hepatic function [see Use in Specific Populations (8.6)]. Also, upon cessation of Argatroban in sodium chloride injection in the hepatically impaired patient, full reversal of anticoagulant effects may require longer than 4 hours due to decreased clearance and increased elimination half-life of argatroban [see Dosage and Administration (2.4) and Clinical Pharmacology (12.3)]. Avoid the use of high doses of Argatroban in sodium chloride injection in patients undergoing PCI who have clinically significant hepatic disease or AST/ALT levels ≥3 times the upper limit of normal.

5.3 Laboratory Tests

Anticoagulation effects associated with Argatroban in sodium chloride injection at doses up to 40 mcg/kg/min correlate with increases of the activated partial thromboplastin time (aPTT). Although other global clot-based tests including prothrombin time (PT), the International Normalized Ratio (INR), and thrombin time (TT) are affected by Argatroban in sodium chloride injection, the therapeutic ranges for these tests have not been identified for Argatroban in sodium chloride injection therapy. In clinical trials in PCI, the activated clotting time (ACT) was used for monitoring argatroban anticoagulant activity during the procedure. The concomitant use of Argatroban in sodium chloride injection and warfarin results in prolongation of the PT and INR beyond that produced by warfarin alone [see Dosage and Administration (2.5) and Clinical Pharmacology (12.2)].

6 ADVERSE REACTIONS

The following serious adverse reactions are described elsewhere in the labeling:

- Risk of Hemorrhage [see Warnings and Precautions (5.1)]

6.1 Clinical Trials Experience

Adverse Reactions in Patients with HIT (With or Without Thrombosis)

Because clinical trials are conducted under widely varying conditions, adverse reaction rates observed in the clinical trials of a drug cannot be directly compared to rates in the clinical trials of another drug and may not reflect the rates observed in practice.

The following safety information is based on all 568 patients treated with argatroban in Study 1 and Study 2. The safety profile of the patients from these studies is compared with that of 193 historical controls in which the adverse reactions were collected retrospectively. Adverse reactions are separated into hemorrhagic and non-hemorrhagic reactions.

Major bleeding was defined as bleeding that was overt and associated with a hemoglobin decrease ≥2 g/dL, that led to a transfusion of ≥2 units, or that was intracranial, retroperitoneal, or into a major prosthetic joint. Minor bleeding was overt bleeding that did not meet the criteria for major bleeding.

Table 4 gives an overview of the most frequently observed hemorrhagic adverse reactions, presented separately by major and minor bleeding, sorted by decreasing occurrence among argatroban-treated patients with HIT (with or without thrombosis).

Table 4.
Major and Minor Hemorrhagic Adverse Reactions in Patients With HIT^1
Major Hemorrhagic Reactions^2
 | Argatroban-Treated Patients (Study 1 and Study 2) (n = 568) % | Historical Control^4 (n = 193) %
Overall bleeding | 5.3 | 6.7
Gastrointestinal | 2.3 | 1.6
Genitourinary and hematuria | 0.9 | 0.5
Decrease in hemoglobin and hematocrit | 0.7 | 0
Multisystem hemorrhage and DIC | 0.5 | 1
Limb and BKA stump | 0.5 | 0
Intracranial hemorrhage | 0^3 | 0.5
Minor Hemorrhagic Reactions^2
 | Argatroban-Treated Patients (Study 1 and Study 2) (n = 568) % | Historical Control^4 (n = 193) %
Gastrointestinal | 14.4 | 18.1
Genitourinary and hematuria | 11.6 | 0.8
Decrease in hemoglobin and hematocrit | 10.4 | 0
Groin | 5.4 | 3.1
Hemoptysis | 2.9 | 0.8
Brachial | 2.4 | 0.8
DIC = disseminated intravascular coagulation.
BKA = below-the-knee amputation.
1. with or without thrombosis
2. Patients may have experienced more than 1 adverse reaction.
3. One patient experienced intracranial hemorrhage 4 days after discontinuation of argatroban and following therapy with urokinase and oral anticoagulation.
4. The historical control group consisted of patients with a clinical diagnosis of HIT (with or without thrombosis) that were considered eligible by an independent medical panel.

Table 5 gives an overview of the most frequently observed non-hemorrhagic reactions sorted by decreasing frequency of occurrence (≥2%) among argatroban-treated HIT/HITTS patients.

Table 5.
Non-hemorrhagic Adverse Reactions in Patients^1 With HIT^2
 | Argatroban-Treated Patients (Study 1 and Study 2) (n = 568) % | Historical Control^3 (n = 193) %
Dyspnea | 8.1 | 8.8
Hypotension | 7.2 | 2.6
Fever | 6.9 | 2.1
Diarrhea | 6.2 | 1.6
Sepsis | 6.0 | 12.4
Cardiac arrest | 5.8 | 3.1
Nausea | 4.8 | 0.5
Ventricular tachycardia | 4.8 | 3.1
Pain | 4.6 | 3.1
Urinary tract infection | 4.6 | 5.2
Vomiting | 4.2 | 0
Infection | 3.7 | 3.6
Pneumonia | 3.3 | 9.3
Atrial fibrillation | 3.0 | 11.4
Coughing | 2.8 | 1.6
Abnormal renal function | 2.8 | 4.7
Abdominal pain | 2.6 | 1.6
Cerebrovascular disorder | 2.3 | 4.1
1. Patients may have experienced more than 1 adverse reaction.
2. With or without thrombosis
3. The historical control group consisted of patients with a clinical diagnosis of HIT (with or without thrombosis) that were considered eligible by an independent medical panel

Adverse Reactions in Patients with or at Risk for HIT Patients Undergoing PCI

The following safety information is based on 91 patients initially treated with argatroban and 21 patients subsequently re-exposed to argatroban for a total of 112 PCIs with argatroban anticoagulation. Adverse reactions are separated into hemorrhagic (Table 6) and non-hemorrhagic (Table 7) reactions.

Major bleeding was defined as bleeding that was overt and associated with a hemoglobin decrease ≥5 g/dL, that led to a transfusion of ≥2 units, or that was intracranial, retroperitoneal, or into a major prosthetic joint.

The rate of major bleeding reactions in patients treated with argatroban in the PCI trials was 1.8%.

Table 6.
Major and Minor Hemorrhagic Adverse Reactions in Patients With HIT Undergoing PCI
Major Hemorrhagic Reactions^1
 | Argatroban-Treated Patients (n = 112)^2 %
Retroperitoneal | 0.9
Gastrointestinal | 0.9
Intracranial | 0
Minor Hemorrhagic Reactions^1
 | Argatroban-Treated Patients (n = 112)^2 %
Groin (bleeding or hematoma) | 3.6
Gastrointestinal (includes hematemesis) | 2.6
Genitourinary (includes hematuria) | 1.8
Decrease in hemoglobin and/or hematocrit | 1.8
CABG (coronary arteries) | 1.8
Access site | 0.9
Hemoptysis | 0.9
Other | 0.9
CABG = coronary artery bypass graft.
1. Patients may have experienced more than 1 adverse reaction.
2. 91 patients who underwent 112 interventions.

Table 7 gives an overview of the most frequently observed non-hemorrhagic adverse reactions (>2%), sorted by decreasing frequency of occurrence among argatroban-treated PCI patients.

Table 7.
Non-hemorrhagic Adverse Reactions^1 in Patients With HIT Undergoing PCI
 | Argatroban Procedures^1 (n = 112)^2 %
Chest pain | 15.2
Hypotension | 10.7
Back pain | 8.0
Nausea | 7.1
Vomiting | 6.3
Headache | 5.4
Bradycardia | 4.5
Abdominal pain | 3.6
Fever | 3.6
Myocardial infarction | 3.6
1. Patients may have experienced more than 1 adverse reaction.
2. 91 patients who underwent 112 interventions.

There were 22 serious adverse reactions in 17 PCI patients (19.6% in 112 interventions). Table 8 lists the serious adverse reactions occurring in argatroban-treated patients with or at risk for HIT undergoing PCI.

Table 8.
Serious Adverse Reactions in Patients With HIT Undergoing PCI^1
Coded Term | Argatroban Procedures^2 (n = 112)
Myocardial infarction | 4 (3.5%)
Angina pectoris | 2 (1.8%)
Coronary thrombosis | 2 (1.8%)
Myocardial ischemia | 2 (1.8%)
Occlusion coronary | 2 (1.8%)
Chest pain | 1 (0.9%)
Fever | 1 (0.9%)
Retroperitoneal hemorrhage | 1 (0.9%)
Aortic stenosis | 1 (0.9%)
Arterial thrombosis | 1 (0.9%)
Gastrointestinal hemorrhage | 1 (0.9%)
Gastrointestinal disorder (GERD) | 1 (0.9%)
Cerebrovascular disorder | 1 (0.9%)
Lung edema | 1 (0.9%)
Vascular disorder | 1 (0.9%)
1. Individual adverse reactions may also have been reported elsewhere (see Table 6 and 7).
2. 91 patients underwent 112 procedures. Some patients may have experienced more than 1 adverse reaction.

Intracranial Bleeding in Other Populations
Increased risks for intracranial bleeding have been observed in investigational studies of argatroban for other uses. In a study of patients with acute myocardial infarction receiving both argatroban and thrombolytic therapy (streptokinase or tissue plasminogen activator), the overall frequency of intracranial bleeding was 1% (8 out of 810 patients). Intracranial bleeding was not observed in 317 subjects or patients who did not receive concomitant thrombolysis [see Drug Interactions (7.4)].
The safety and effectiveness of Argatroban in sodium chloride injection for cardiac indications other than PCI in patients with HIT have not been established. Intracranial bleeding was also observed in a prospective, placebo-controlled study of argatroban in patients who had onset of acute stroke within 12 hours of study entry. Symptomatic intracranial hemorrhage was reported in 5 of 117 patients (4.3%) who received argatroban at 1 to 3 mcg/kg/min and in none of the 54 patients who received placebo. Asymptomatic intracranial hemorrhage occurred in 5 (4.3%) and 2 (3.7%) of the patients, respectively.
Allergic Reactions

One hundred fifty-six allergic reactions or suspected allergic reactions were observed in 1,127 individuals who were treated with argatroban in clinical pharmacology studies or for various clinical indications. About 95% (148/156) of these reactions occurred in patients who concomitantly received thrombolytic therapy (e.g., streptokinase) or contrast media.

Allergic reactions or suspected allergic reactions in populations other than patients with HIT (with or without thrombosis) include (in descending order of frequency):

• Airway reactions (coughing, dyspnea): 10% or more

• Skin reactions (rash, bullous eruption): 1 to <10%

• General reactions (vasodilation): 1 to 10%

Limited data are available on the potential formation of drug-related antibodies. Plasma from 12 healthy volunteers treated with argatroban over 6 days showed no evidence of neutralizing antibodies. No loss of anticoagulant activity was noted with repeated administration of argatroban to more than 40 patients.

7 DRUG INTERACTIONS

7.1 Heparin

If Argatroban in sodium chloride injection is to be initiated after cessation of heparin therapy, allow sufficient time for heparin’s effect on the aPTT to decrease prior to initiation of Argatroban in sodium chloride injection therapy.

7.2 Oral Anticoagulant Agents

Pharmacokinetic drug-drug interactions between Argatroban in sodium chloride injection and warfarin (7.5 mg single oral dose) have not been demonstrated. However, the concomitant use of Argatroban in sodium chloride injection and warfarin (5 to 7.5 mg initial oral dose, followed by 2.5 to 6 mg/day orally for 6 to 10 days) results in prolongation of the prothrombin time (PT) and International Normalized Ratio (INR) [see Dosage and Administration (2.5), Clinical Pharmacology (12.2)].

7.3 Aspirin/Acetaminophen

No drug-drug interactions have been demonstrated between Argatroban in sodium chloride injection and concomitantly administered aspirin or acetaminophen [see Clinical Pharmacology (12.3)].

7.4 Thrombolytic Agents

The safety and effectiveness of Argatroban in sodium chloride injection with thrombolytic agents have not been established [see Adverse Reactions (6.1)].

7.5 Glycoprotein IIb/IIIa Antagonists

The safety and effectiveness of Argatroban in sodium chloride injection with glycoprotein IIb/IIIa antagonists have not been established.

8 USE IN SPECIFIC POPULATIONS

8.1 Pregnancy

Risk Summary
Limited data from published literature and postmarketing reports do not suggest an association between Argatroban in sodium chloride injection and adverse fetal developmental outcomes. There are risks to the mother associated with untreated thrombosis in pregnancy and a risk of hemorrhage in the mother and fetus associated with use of anticoagulants (see Clinical Considerations). In animal reproduction studies, there was no evidence of adverse developmental outcomes with intravenous administration of argatroban during organogenesis in rats and rabbits at doses up to 0.3- and 0.2 times, respectively, the maximum recommended human dose (MHRD) (see Data).
The estimated background risk of major birth defects and miscarriage for the indicated population is unknown. All pregnancies have a background risk of birth defect, loss, or other adverse outcomes. In the U.S. general population, the estimated background risk of birth defects and miscarriage in clinically recognized pregnancies is 2%-4% and 15%-20%, respectively.

Clinical Considerations

Disease-Associated Maternal and/or Embryo-Fetal Risk
Pregnancy confers an increased risk for thromboembolism that is higher for women with underlying thromboembolic disease and certain high risk pregnancy conditions. Published data describe that women with a previous history of venous thrombosis are at high risk for recurrence during pregnancy.
Fetal/Neonatal Adverse Reactions
Use of anticoagulants, including Argatroban in sodium chloride injection, may increase the risk of bleeding in the fetus and neonate. Monitor neonates for bleeding [see Warnings and Precautions (5.1, 5.3)].
Labor or Delivery
All patients receiving anticoagulants, including pregnant women, are at risk for bleeding. Pregnant women receiving Argatroban in sodium chloride injection should be carefully monitored for evidence of excessive bleeding or unexpected changes in coagulation parameters [see Warnings and Precautions (5.1, 5.3)].

Data

Animal Data
Developmental studies performed in rats with argatroban at intravenous doses up to 27 mg/kg/day (0.3 times the maximum recommended human dose, based on body surface area) and in rabbits at intravenous doses up to 10.8 mg/kg/day (0.2 times the maximum recommended dose for humans, based on body surface area) have revealed no evidence of harm to the fetus.

8.2 Lactation

Risk Summary
There are no data on the presence of argatroban in human milk, or its effects on milk production. Argatroban is present in rat milk. The developmental and health benefits of breastfeeding should be considered along with the mother’s need for Argatroban in sodium chloride injection and any potential adverse effects on the breastfed child from Argatroban in sodium chloride injection or from the underlying maternal condition.
Data
Animal Data
Argatroban is detected in rat milk.

8.4 Pediatric Use

Safety and effectiveness have not been established in pediatric patients.
Argatroban was studied among 18 seriously ill pediatric patients who required an alternative to heparin anticoagulation. Most patients were diagnosed with HIT or suspected HIT. Age ranges of patients were <6 months, n = 8; six months to <8 years, n = 6; 8 to 16 years, n = 4. All patients had serious underlying conditions and were receiving multiple concomitant medications. Thirteen patients received argatroban solely as a continuous infusion (no bolus dose). Dosing was initiated in the majority of these 13 patients at 1 mcg/kg/min and subsequently titrated as needed to achieve and maintain an aPTT of 1.5 to 3 times the baseline value. Most patients required multiple dose adjustments to maintain anticoagulation parameters within the desired range. During the 30-day study period, thrombotic events occurred during argatroban administration to two patients and following argatroban discontinuation in three other patients. Major bleeding occurred among two patients; one patient experienced an intracranial hemorrhage after 4 days of argatroban therapy in the setting of sepsis and thrombocytopenia and another patient experienced an intracranial hemorrhage after receiving argatroban for greater than 14 days. The study findings did not establish the safe and effective use of argatroban in pediatric patients and the dosing of 1 mcg/kg/min was not supported by the pharmacokinetic data described below.
Pediatric Pharmacokinetics (PK) and Pharmacodynamics (PD)
PK parameters of argatroban were characterized in population PK/PD analysis model with sparse data from 15 seriously ill pediatric patients. Argatroban clearance in these seriously ill pediatric patients (0.16 L/hr/kg) was 50% lower compared to argatroban clearance in healthy adults (0.31 L/hr/kg). Four pediatric patients with elevated bilirubin (secondary to cardiac complications or hepatic impairment) had, on average, 80% lower clearance (0.03 L/hr/kg) when compared to pediatric patients with normal bilirubin levels.
These PK/PD analysis models based on a goal of aPTT prolongation of 1.5 to 3 times the baseline value and avoidance of an aPTT >100 seconds for seriously ill pediatric patients with HIT/HITTS who require an alternative to heparin suggested the following:

- For patients with normal hepatic function, a starting infusion rate of 0.75 mcg/kg/min may have comparable aPTT responses as a starting dose of 2 mcg/kg/min in healthy adults. Additionally, based on an evaluation of aPTT every two hours, increasing the dosage by 0.1 to 0.25 mcg/kg/min could achieve additional aPTT responses.
- For patients with hepatic impairment a starting infusion rate of 0.2 mcg/kg/min with increasing dosing by increments of 0.05 mcg/kg/min may have comparable argatroban exposure as expected with adult doses.

The safety and effectiveness of Argatroban in sodium chloride injection with the above dosing have not been adequately assessed in pediatric patients and the safety and effectiveness of Argatroban in sodium chloride injection is not established in pediatric patients. In addition, the described dosage did not take into account multiple factors that could affect the dosage such as current aPTT, target aPTT, and the clinical status of the patient.

8.5 Geriatric Use

Of the total number of subjects (1340) in clinical studies of argatroban, 35% were 65 and over. In the clinical studies of adult patients with HIT (with or without thrombosis), the effectiveness of argatroban was not affected by age. No trends were observed across age groups for both aPTT and the ACT. The safety analysis did suggest that older patients tended to have an increased incidence of adverse reactions compared to younger patients; however, older patients had increased underlying conditions, which may predispose them to adverse reactions. The studies were not sized appropriately to detect differences in safety between age groups.

8.6 Hepatic Impairment

Dose reduction and careful titration are required when administering Argatroban in sodium chloride injection to patients with hepatic impairment. Reversal of anticoagulation effect may be prolonged in this population [see Dosage and Administration (2.4), Warnings and Precautions (5.2), Clinical Pharmacology (12.3)].

10 OVERDOSAGE

Excessive anticoagulation, with or without bleeding, may be controlled by discontinuing Argatroban in sodium chloride injection or by decreasing the Argatroban in sodium chloride injection dose. In clinical studies, anticoagulation parameters generally returned from therapeutic levels to baseline within 2 to 4 hours after discontinuation of the drug. Reversal of anticoagulant effect may take longer in patients with hepatic impairment.
No specific antidote to Argatroban in sodium chloride injection is available; if life-threatening bleeding occurs and excessive plasma levels of argatroban are suspected, discontinue Argatroban in sodium chloride injection immediately and measure aPTT and other coagulation parameters. When argatroban was administered as a continuous infusion (2 mcg/kg/min) prior to and during a 4-hour hemodialysis session, approximately 20% of argatroban was cleared through dialysis.
Single intravenous doses of argatroban at 200, 124, 150, and 200 mg/kg were lethal to mice, rats, rabbits, and dogs, respectively. The symptoms of acute toxicity were loss of righting reflex, tremors, clonic convulsions, paralysis of hind limbs, and coma.

11 DESCRIPTION

Argatroban in sodium chloride injection is a synthetic direct thrombin inhibitor.
The chemical name for argatroban monohydrate is 1-[5-[(aminoiminomethyl)amino]-1-oxo-2-[[(1,2,3,4-tetrahydro-3-methyl-8-quinolinyl)sulfonyl]amino]pentyl]-4-methyl-2-piperidinecarboxylic acid, monohydrate. Argatroban has 4 asymmetric carbons. One of the asymmetric carbons has an R configuration (stereoisomer Type I) and an S configuration (stereoisomer Type II). Argatroban consists of a mixture of R and S stereoisomers at a ratio of approximately 65:35.
The molecular formula of argatroban is C23H36N6O5S•H2O. Its molecular weight is 526.66 g/mol. The structural formula is:
Argatroban in sodium chloride injection is a sterile, non-pyrogenic, clear, colorless to pale yellow solution. It is supplied in a clear glass single-dose vial containing 50 mg of argatroban in 50 mL sodium chloride solution. Each mL contains 1 mg argatroban, 9 mg sodium chloride, USP, 3 mg sorbitol, NF in water for injection, USP. The pH of the solution is between 4.0 to 7.5.

12 CLINICAL PHARMACOLOGY

12.1 Mechanism of Action

Argatroban in sodium chloride injection is a direct thrombin inhibitor that reversibly binds to the thrombin active site. Argatroban does not require the co-factor antithrombin III for antithrombotic activity. Argatroban exerts its anticoagulant effects by inhibiting thrombin-catalyzed or -induced reactions, including fibrin formation; activation of coagulation factors V, VIII, and XIII; activation of protein C; and platelet aggregation.
Argatroban inhibits thrombin with an inhibition constant (Ki) of 0.04 μM. At therapeutic concentrations, argatroban has little or no effect on related serine proteases (trypsin, factor Xa, plasmin, and kallikrein).
Argatroban is capable of inhibiting the action of both free and clot-associated thrombin.

12.2 Pharmacodynamics

When argatroban is administered by continuous infusion, anticoagulant effects and plasma concentrations of argatroban follow similar, predictable temporal response profiles, with low intersubject variability. Immediately upon initiation of argatroban infusion, anticoagulant effects are produced as plasma argatroban concentrations begin to rise. Steady-state levels of both drug and anticoagulant effect are typically attained within 1 to 3 hours and are maintained until the infusion is discontinued or the dosage adjusted. Steady-state plasma argatroban concentrations increase proportionally with dose (for infusion doses up to 40 mcg/kg/min in healthy subjects) and are well correlated with steady-state anticoagulant effects. For infusion doses up to 40 mcg/kg/min, argatroban increases in a dose-dependent fashion, the activated partial thromboplastin time (aPTT), the activated clotting time (ACT), the prothrombin time (PT), the International Normalized Ratio (INR), and the thrombin time (TT) in healthy volunteers and cardiac patients. Representative steady-state plasma argatroban concentrations and anticoagulant effects are shown below for argatroban infusion doses up to 10 mcg/kg/min (see Figure 1).
Effect on International Normalized Ratio (INR): Because argatroban is a direct thrombin inhibitor, co-administration of argatroban and warfarin produces a combined effect on the laboratory measurement of the INR. However, concurrent therapy, compared to warfarin monotherapy, exerts no additional effect on vitamin K–dependent factor Xa activity.
The relationship between INR on co-therapy and warfarin alone is dependent on both the dose of argatroban and the thromboplastin reagent used. This relationship is influenced by the International Sensitivity Index (ISI) of the thromboplastin. Data for 2 commonly utilized thromboplastins with ISI values of 0.88 (Innovin, Dade) and 1.78 (Thromboplastin C Plus, Dade) are presented in Figure 2 for an argatroban dose of 2 mcg/kg/min. Thromboplastins with higher ISI values than shown result in higher INRs on combined therapy of warfarin and argatroban. These data are based on results obtained in normal individuals [see Dosage and Administration (2.5), Warnings and Precautions (5.3)].
Figure 2 demonstrates the relationship between INR for warfarin alone and INR for warfarin co-administered with argatroban at a dose of 2 mcg/kg/min. To calculate INR for warfarin alone (INRW), based on INR for co-therapy of warfarin and argatroban (INRWA), when the argatroban dose is 2 mcg/kg/min, use the equation next to the appropriate curve. Example: At a dose of 2 mcg/kg/min and an INR performed with Thromboplastin A, the equation 0.19 + 0.57 (INRWA) = INRW would allow a prediction of the INR on warfarin alone (INRW). Thus, using an INRWA value of 4.0 obtained on combined therapy: INRW = 0.19 + 0.57 (4) = 2.47 as the value for INR on warfarin alone. The error (confidence interval) associated with a prediction is ± 0.4 units. Similar linear relationships and prediction errors exist for argatroban at a dose of 1 mcg/kg/min. Thus, for argatroban doses of 1 or 2 mcg/kg/min, INRW can be predicted from INRWA. For argatroban doses greater than 2 mcg/kg/min, the error associated with predicting INRW from INRWA is ± 1. Thus, INRW cannot be reliably predicted from INRWA at doses greater than 2 mcg/kg/min.

12.3 Pharmacokinetics

Distribution:
Argatroban distributes mainly in the extra cellular fluid as evidenced by an apparent steady-state volume of distribution of 174 mL/kg (12.18 L in a 70 kg adult). Argatroban is 54% bound to human serum proteins, with binding to albumin and α1-acid glycoprotein being 20% and 34%, respectively.
Metabolism:
The main route of argatroban metabolism is hydroxylation and aromatization of the 3-methyltetrahydroquinoline ring in the liver. The formation of each of the 4 known metabolites is catalyzed in vitro by the human liver microsomal cytochrome P450 enzymes CYP3A4/5. The primary metabolite (M1) exerts 3- to 5-fold weaker anticoagulant effects than argatroban. Unchanged argatroban is the major component in plasma. The plasma concentrations of M1 range between 0% and 20% of that of the parent drug. The other metabolites (M2 to M4) are found only in very low quantities in the urine and have not been detected in plasma or feces. These data, together with the lack of effect of erythromycin (a potent CYP3A4/5 inhibitor) on argatroban pharmacokinetics, suggest that CYP3A4/5-mediated metabolism is not an important elimination pathway in vivo.
Total body clearance is approximately 5.1 mL/kg/min (0.31 L/kg/hr) for infusion doses up to 40 mcg/kg/min. The terminal elimination half-life of argatroban ranges between 39 and 51 minutes.
There is no interconversion of the 21–(R):21–(S) diastereoisomers. The plasma ratio of these diastereoisomers is unchanged by metabolism or hepatic impairment, remaining constant at 65:35 (± 2%).
Excretion:
Argatroban is excreted primarily in the feces, presumably through biliary secretion. In a study in which ^14C-argatroban (5 mcg/kg/min) was infused for 4 hours into healthy subjects, approximately 65% of the radioactivity was recovered in the feces within 6 days of the start of infusion with little or no radioactivity subsequently detected. Approximately 22% of the radioactivity appeared in the urine within 12 hours of the start of infusion. Little or no additional urinary radioactivity was subsequently detected. Average percent recovery of unchanged drug, relative to total dose, was 16% in urine and at least 14% in feces.
Special Populations:
Hepatic Impairment: The dosage of Argatroban in sodium chloride injection should be decreased in patients with hepatic impairment [see Dosage and Administration (2.4) and Warnings and Precautions (5.2)]. Patients with hepatic impairment were not studied in percutaneous coronary intervention (PCI) trials. At a dose of 2.5 mcg/kg/min, hepatic impairment is associated with decreased clearance and increased elimination half-life of argatroban (to 1.9 mL/kg/min and 181 minutes, respectively, for patients with a Child-Pugh score >6).
Renal Impairment: No dosage adjustment is necessary in patients with renal dysfunction. The effect of renal disease on the pharmacokinetics of argatroban was studied in 6 subjects with normal renal function (mean Clcr = 95 ± 16 mL/min) and in 18 subjects with mild (mean Clcr = 64 ± 10 mL/min), moderate (mean Clcr = 41 ± 5.8 mL/min), and severe (mean Clcr = 5 ± 7 mL/min) renal impairment. The pharmacokinetics and pharmacodynamics of argatroban at dosages up to 5 mcg/kg/min were not significantly affected by renal dysfunction.
Use of argatroban was evaluated in a study of 12 patients with stable end-stage renal disease undergoing chronic intermittent hemodialysis. Argatroban was administered at a rate of 2 to 3 mcg/kg/min (begun at least 4 hours prior to dialysis) or as a bolus dose of 250 mcg/kg at the start of dialysis followed by a continuous infusion of 2 mcg/kg/min. Although these regimens did not achieve the goal of maintaining ACT values at 1.8 times the baseline value throughout most of the hemodialysis period, the hemodialysis sessions were successfully completed with both of these regimens. The mean ACTs produced in this study ranged from 1.39 to 1.82 times baseline, and the mean aPTTs ranged from 1.96 to 3.4 times baseline. When argatroban was administered as a continuous infusion of 2 mcg/kg/min prior to and during a 4-hour hemodialysis session, approximately 20% was cleared through dialysis.
Age, Gender: There are no clinically significant effects of age or gender on the pharmacokinetics or pharmacodynamics (e.g., aPTT) of argatroban in adults.
Drug-Drug Interactions:
Digoxin: In 12 healthy volunteers, intravenous infusion of argatroban (2 mcg/kg/min) over 5 days (study days 11 to 15) did not affect the steady-state pharmacokinetics of oral digoxin (0.375 mg daily for 15 days).
Erythromycin: In 10 healthy subjects, orally administered erythromycin (a potent inhibitor of CYP3A4/5) at 500 mg four times daily for 7 days had no effect on the pharmacokinetics of argatroban at a dose of 1 mcg/kg/min for 5 hours. These data suggest oxidative metabolism by CYP3A4/5 is not an important elimination pathway in vivo for argatroban.
Aspirin and Acetaminophen: Drug-drug interactions have not been demonstrated between argatroban and concomitantly administered aspirin (162.5 mg orally given 26 and 2 hours prior to initiation of argatroban 1 mcg/kg/min over 4 hours) or acetaminophen (1,000 mg orally given 12, 6, and 0 hours prior to, and 6 and 12 hours subsequent to, initiation of argatroban 1.5 mcg/kg/min over 18 hours).

13 NONCLINICAL TOXICOLOGY

13.1 Carcinogenesis, Mutagenesis, Impairment of Fertility

Carcinogenicity studies with argatroban have not been performed.
Argatroban was not genotoxic in the Ames test, the Chinese hamster ovary cell (CHO/HGPRT) forward mutation test, the Chinese hamster lung fibroblast chromosome aberration test, the rat hepatocyte, and WI-38 human fetal lung cell unscheduled DNA synthesis (UDS) tests, or the mouse micronucleus test.
Argatroban at intravenous doses up to 27 mg/kg/day (0.3 times the recommended maximum human dose based on body surface area) had no effect on fertility and reproductive function of male and female rats.

14 CLINICAL STUDIES

14.1 Heparin-Induced Thrombocytopenia

The safety and efficacy of argatroban were evaluated in an historically controlled efficacy and safety study (Study 1) and a follow-on efficacy and safety study (Study 2). These studies were comparable with regard to study design, study objectives, dosing regimens as well as study outline, conduct, and monitoring.
In these studies, 568 adult patients were treated with argatroban and 193 adult patients made up the historical control group. Patients had a clinical diagnosis of heparin-induced thrombocytopenia, either without thrombosis (HIT) or with thrombosis (HITTS [heparin-induced thrombocytopenia and thrombosis syndrome]) and were males or non-pregnant females between the age of 18 and 80 years old. HIT/HITTS was defined by a fall in platelet count to less than 100,000/μL or a 50% decrease in platelets after the initiation of heparin therapy with no apparent explanation other than HIT. Patients with HITTS also had an arterial or venous thrombosis documented by appropriate imaging techniques or supported by clinical evidence such as acute myocardial infarction, stroke, pulmonary embolism, or other clinical indications of vascular occlusion. Patients who had documented histories of positive heparin-dependent antibody tests without current thrombocytopenia or heparin challenge (e.g., patients with latent disease) were also included if they required anticoagulation.
These studies did not include patients with documented unexplained aPTT >200% of control at baseline, documented coagulation disorder or bleeding diathesis unrelated to HIT, a lumbar puncture within the past 7 days or a history of previous aneurysm, hemorrhagic stroke, or a thrombotic stroke within the past 6 months unrelated to HIT.
The initial dose of argatroban was 2 mcg/kg/min. Two hours after the start of the argatroban infusion, an aPTT level was obtained and dose adjustments were made (up to a maximum of 10 mcg/kg/min) to achieve a steady-state aPTT value that was 1.5 to 3.0 times the baseline value, not to exceed 100 seconds. Overall the mean aPTT level for HIT and HITTS patients during the Argatroban infusion increased from baseline values of 34 and 38 seconds, respectively, to 62.5 and 64.5 seconds, respectively.
The primary efficacy analysis was based on a comparison of event rates for a composite endpoint that included death (all causes), amputation (all causes) or new thrombosis during the treatment and follow-up period (study days 0 to 37).
Secondary analyses included evaluation of the event rates for the components of the composite endpoint as well as time-to-event analyses.
In Study 1, a total of 304 patients were enrolled as follows: active HIT (n = 129), active HITTS (n = 144), or latent disease (n = 31). Among the 193 historical controls, 139 (72%) had active HIT, 46 (24%) had active HITTS, and 8 (4%) had latent disease. Within each group, those with active HIT and those with latent disease were analyzed together. Positive laboratory confirmation of HIT/HITTS by the heparin-induced platelet aggregation test or serotonin release assay was demonstrated in 174 of 304 (57%) argatroban-treated patients (i.e., in 80 with HIT or latent disease and 94 with HITTS) and in 149 of 193 (77%) historical controls (i.e., in 119 with HIT or latent disease and 30 with HITTS). The test results for the remainder of the patients and controls were either negative or not determined.
There was a significant improvement in the composite outcome in patients with HIT and HITTS treated with argatroban versus those in the historical control group (see Table 9). The components of the composite endpoint are shown in Table 9.

Table 9.
Efficacy Results of Study 1: Composite Endpoint^1 and Individual Components, Ranked by Severity^2
 | HIT |  | HITTS |  | HIT/HITTS
Parameter, N (%) | Control n = 147 | Argatroban n = 160 | Control n = 46 | Argatroban n = 144 | Control n = 193 | Argatroban n = 304
Composite Endpoint | 57 (38.8) | 41 (25.6) | 26 (56.5) | 63 (43.8) | 83 (43.0) | 104 (34.2)
Individual Components^2:
Death | 32 (21.8) | 27 (16.9) | 13 (28.3) | 26 (18.1) | 45 (23.3) | 53 (17.4)
Amputation | 3 (2.0) | 3 (1.9) | 4 (8.7) | 16 (11.1) | 7 (3.6) | 19 (6.2)
New Thrombosis | 22 (15.0) | 11 (6.9) | 9 (19.6) | 21 (14.6) | 31 (16.1) | 32 (10.5)
1. Death (all cause), amputation (all cause), or new thrombosis within 37-day study period
2. Reported as the most severe outcome among the components of composite endpoint (severity ranking: death > amputation > new thrombosis); patients may have had multiple outcomes.

Time-to-event analyses showed significant improvements in the time-to-first event in patients with HIT or HITTS treated with argatroban versus those in the historical control group. The between-group differences in the proportion of patients who remained free of death, amputation, or new thrombosis were statistically significant in favor of argatroban by these analyses.
A time-to-event analysis for the composite endpoint is shown in Figure 3 for patients with HIT and Figure 4 for patients with HITTS.
In Study 2, a total of 264 patients were enrolled as follows: HIT (n = 125) or HITTS (n = 139). There was a significant improvement in the composite efficacy outcome for argatroban-treated patients, versus the same historical control group from Study 1, among patients having HIT (25.6% vs. 38.8%), patients having HITTS (41.0% vs. 56.5%), and patients having either HIT or HITTS (33.7% vs. 43.0%). Time-to-event analyses showed significant improvements in the time-to-first event in patients with HIT or HITTS treated with argatroban versus those in the historical control group. The between-group differences in the proportion of patients who remained free of death, amputation, or new thrombosis were statistically significant in favor of argatroban.
Anticoagulant Effect:
In Study 1, the mean (± SE) dose of argatroban administered was 2.0 ± 0.1 mcg/kg/min in the HIT arm and 1.9 ± 0.1 mcg/kg/min in the HITTS arm. Seventy-six percent of patients with HIT and 81% of patients with HITTS achieved a target aPTT at least 1.5-fold greater than the baseline aPTT at the first assessment occurring on average at 4.6 hours (HIT) and 3.9 hours (HITTS) following initiation of argatroban therapy.
No enhancement of aPTT response was observed in subjects receiving repeated administration of argatroban.
Platelet Count Recovery:
In Study 1, 53% of patients with HIT and 58% of patients with HITTS, had a recovery of platelet count by Day 3. Platelet Count Recovery was defined as an increase in platelet count to >100,000/μL or to at least 1.5-fold greater than the baseline count (platelet count at study initiation) by Day 3 of the study.

14.2 Percutaneous Coronary Intervention (PCI) Patients with or at Risk for HIT

In 3 similarly designed trials, argatroban was administered to 91 patients with current or previous clinical diagnosis of HIT or heparin-dependent antibodies, who underwent a total of 112 percutaneous coronary interventions (PCIs) including percutaneous transluminal coronary angioplasty (PTCA), coronary stent placement, or atherectomy.
Among the 91 patients undergoing their first PCI with argatroban, notable ongoing or recent medical history included myocardial infarction (n = 35), unstable angina (n = 23), and chronic angina (n = 34). There were 33 females and 58 males. The average age was 67.6 years (median 70.7, range 44 to 86), and the average weight was 82.5 kg (median 81.0 kg, range 49 to 141).
Twenty-one of the 91 patients had a repeat PCI using argatroban an average of 150 days after their initial PCI. Seven of 91 patients received glycoprotein IIb/IIIa inhibitors. Safety and efficacy were assessed against historical control populations who had been anticoagulated with heparin.
All patients received oral aspirin (325 mg) 2 to 24 hours prior to the interventional procedure. After venous or arterial sheaths were in place, anticoagulation was initiated with a bolus of argatroban of 350 mcg/kg via a large-bore intravenous line or through the venous sheath over 3 to 5 minutes. Simultaneously, a maintenance infusion of 25 mcg/kg/min was initiated to achieve a therapeutic activated clotting time (ACT) of 300 to 450 seconds. If necessary to achieve this therapeutic range, the maintenance infusion dose was titrated (15 to 40 mcg/kg/min) and/or an additional bolus dose of 150 mcg/kg could be given. Each patient’s ACT was checked 5 to 10 minutes following the bolus dose. The ACT was checked as clinically indicated. Arterial and venous sheaths were removed no sooner than 2 hours after discontinuation of argatroban and when the ACT was less than 160 seconds.
If a patient required anticoagulation after the procedure, argatroban could be continued, but at a lower infusion dose between 2.5 and 5 mcg/kg/min. An aPTT was drawn 2 hours after this dose reduction and the dose of argatroban then was adjusted as clinically indicated (not to exceed 10 mcg/kg/min), to reach an aPTT between 1.5 and 3 times baseline value (not to exceed 100 seconds).
In 92 of the 112 interventions (82%), the patient received the initial bolus of 350 mcg/kg and an initial infusion dose of 25 mcg/kg/min. The majority of patients did not require additional bolus dosing during the PCI procedure. The mean value for the initial ACT measurement after the start of dosing for all interventions was 379 sec (median 338 sec; 5th percentile-95th percentile 238 to 675 sec). The mean ACT value per intervention over all measurements taken during the procedure was 416 sec (median 390 sec; 5th percentile-95th percentile 261 to 698 sec). About 65% of patients had ACTs within the recommended range of 300 to 450 seconds throughout the procedure. The investigators did not achieve anticoagulation within the recommended range in about 23% of patients. However, in this small sample, patients with ACTs below 300 seconds did not have more coronary thrombotic events, and patients with ACTs over 450 seconds did not have higher bleeding rates.
Acute procedural success was defined as lack of death, emergent coronary artery bypass graft (CABG), or Q-wave myocardial infarction. Acute procedural success was reported in 98.2% of patients who underwent PCIs with argatroban anticoagulation compared with 94.3% of historical control patients anticoagulated with heparin (p = NS). Among the 112 interventions, 2 patients had emergency CABGs, 3 had repeat PTCAs, 4 had non-Q-wave myocardial infarctions, 3 had myocardial ischemia, 1 had an abrupt closure, and 1 had an impending closure (some patients may have experienced more than 1 event). No patients died.

16 HOW SUPPLIED/STORAGE AND HANDLING

Argatroban in sodium chloride injection is supplied as a single-dose vial containing 50 mg argatroban in 50 mL of aqueous solution (1 mg/mL).
50 mL single-dose vials
packaged in carton of 10 vials NDC 55150-241-10
50 mL single-dose vial
packaged individually NDC 55150-241-01
Storage and Handling:
Store the vials in original cartons at 20º to 25ºC (68º to 77°F); excursions permitted to 15° to 30°C (59° to 86°F) [see USP Controlled Room Temperature]. Do not refrigerate or freeze. Retain in the original carton to protect from light. If the solution is cloudy, or if an insoluble precipitate is noted, the vial should be discarded.
The vial stopper is not made with natural rubber latex.

17 PATIENT COUNSELING INFORMATION

Inform patients of the risks associated with Argatroban in sodium chloride injection as well as the plan for regular monitoring during administration of the drug. Specifically, inform patients to report:

- the use of any other products known to affect bleeding [see Warnings and Precautions (5.1)].
- any medical history that may increase the risk for bleeding, including a history of severe hypertension; recent lumbar puncture or spinal anesthesia; major surgery, especially involving the brain, spinal cord, or eye; hematologic conditions associated with increased bleeding tendencies such as congenital or acquired bleeding disorders and gastrointestinal lesions such as ulcerations.
- any bleeding signs or symptoms.
- the occurrence of any signs or symptoms of allergic reactions (e.g., airway reactions, skin reactions and vasodilation reactions) [see Adverse Reactions (6.1)].

Distributed by:
Eugia US LLC
279 Princeton-Hightstown Rd.
E. Windsor, NJ 08520
Manufactured by:
Eugia Pharma Specialities Limited
Hyderabad - 500032
India

PACKAGE LABEL-PRINCIPAL DISPLAY PANEL - 50 mg per 50 mL (1 mg / mL) - Container Label

Rx only NDC 55150-241-01
Argatroban
in 0.9% Sodium Chloride Injection
50 mg per 50 mL
(1 mg / mL)
For Intravenous Infusion Only
Do not dilute prior to administration
Discard Unused Portion
50 mL Single Dose Vial

PACKAGE LABEL-PRINCIPAL DISPLAY PANEL - 50 mg per 50 mL (1 mg / mL) - Container-Carton

Rx only NDC 55150-241-01
Argatroban
in 0.9% Sodium Chloride Injection
50 mg per 50 mL
(1 mg/mL)
For Intravenous Infusion Only
Do not dilute prior to administration
Discard Unused Portion
Sterile Non-pyrogenic
50 mL Single-Dose Vial
eugia

PACKAGE LABEL-PRINCIPAL DISPLAY PANEL - 50 mg per 50 mL (1 mg / mL) – Container-Carton (10 Vials)

Rx only NDC 55150-241-10
Argatroban
in 0.9% Sodium Chloride Injection
50 mg per 50 mL
(1 mg / mL)
For Intravenous Infusion Only
Do not dilute prior to administration
Discard Unused Portion
Sterile 10 x 50 mL
Non-pyrogenic Single Dose Vials
eugia